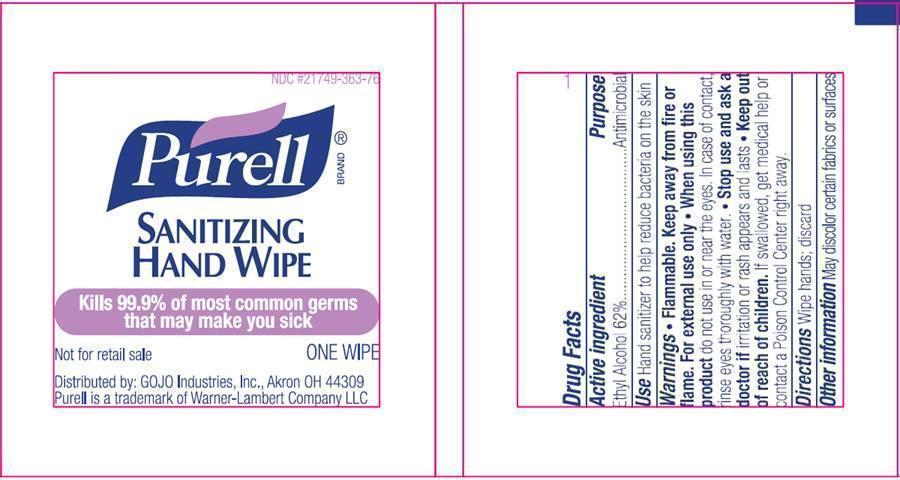 DRUG LABEL: Stool collection kit for GI molecular test
NDC: 70049-211 | Form: KIT | Route: TOPICAL
Manufacturer: H&M MEDICAL COLLECTION KITS LLC
Category: other | Type: MEDICAL DEVICE
Date: 20150901

ACTIVE INGREDIENTS: ALCOHOL 0.62 mL/1 mL
INACTIVE INGREDIENTS: WATER; ISOPROPYL ALCOHOL; ALOE VERA LEAF; C12-15 ALKYL BENZOATE; GLYCERIN; ISOPROPYL MYRISTATE; PROPYLENE GLYCOL; VITAMIN A PALMITATE; ALPHA-TOCOPHEROL ACETATE; CORN OIL; AMINOMETHYLPROPANOL; METHYLPARABEN

Stool collection kit for GI molecular test

KIT Includes

- Lab Tissue Mailer, Overall Height 3-7/8 In., Overall Length 4-1/8 In., Zoro Number: G3670484, Mfr Number: 729/CP; Qty-1
- "Mini Ice Pack from an Ice pack Sqaure Mat, Length 16-1/2 In., Width 14-3/4 In., Height 14-3/4 In., Zoro #: G5830133 | Mfr #: 405SQ (each matt has 60 pieces, which only one small piece is used)
- Mailing Carton, Capacity 72 cu. in., Color White, Inside Width 4 In., Inside Length 6 In., Inside Depth 3 In,Zoro#: G1072556 | Mfr#: 0101-1681010; Qty-1
- One 3ml transfer pipette; Transfer Pipet, 3.0mL, Small Bulb, Graduated to 1mL, 140mm, Bulb Draw - 2.2mL, globe scientific, item#137035; Qty-1
- One pair of medium latex free gloves
- Bag, Biohazard Specimen Transport, 6" x 9", Ziplock with Document Pouch, Globe scientific,item#4919; Qty-1
- Container, Fecal, 30mL, attached Screw Cap with Spoon, PP, Conical Bottom, Self-Standing, globe scientific, item#109120; Qty-1
- Sterile cotton tipped applicators, Dynarexcorporation, 2 X 6"inch, reorder no. 4305, lot: 25519; Qty-1
- Microtube, 1.5mL, Self-Standing, Attached Screw Cap for Color Insert, with O-Ring, STERILE, PP, globe scientific, item#111720; Qty-2
- Alcohol pads: PT# 5110 PT# # 5110- Prep Surgical Alcohol Pads Webcol Large by, Kendall Company Qty: 2 in each kit
- 1A Mini zip lock with a toilet cover seat: The Hospeco Health Gards half-fold toilet seat cover (part number:HG-1000) which is located inside a mini zip lock. Qty:1
- PURELL Sanitizing Hand Wipes Individually Wrapped: Qty;1 in each kit
- Labels for patient identification
- Instruction sheet for collection the sample
- Requisition form for the clinicians

Active ingredient

Ethyl alcohol 62%

Purpose

Antimicrobial

Keep out of reach of children. If swallowed, get medical help or contact a Poison Control Center right away.

INDICATIONS AND USAGE

Use Hand sanitizer to help reduce bacteria on the skin

Warnings

• Flammable. Keep away from fire or flame,

• For external use only

• When using this product do not use in or near the eyes. In case of contact, rinse eyes thoroughly with water.

• Stop use and ask a doctor if irritation or rash appears and lasts

DOSAGE AND ADMINISTRATION

Directions • Unfold towelette; Wipe hands; Discard after use

Other information

- Do not store above 110°F (43°C)
- May discolor certain fabrics or surfaces

Inactive ingredients

Water (Aqua), Isopropyl Alcohol, Acetamidopropyl Trimonium Chloride, Aloe Barbadensis Leaf Juice, C12-15 Alkyl Benzoate, Cocamidopropyl PG-Dimonium Chloride Phosphate, Glycerin, Isopropyl Myristate, Propylene Glycol, Retinyl Palmitate, Tocopheryl Acetate, Zea Mays (Corn) Oil, Acrylates/C10-30 Alkyl Acrylate Crosspolymer, Aminomethyl Propanol, Fragrance (Parfum), Methylparaben

Questions?

1-800-321-9647

PACKAGE INFORMATION

NDC 21749-363-76

Purell Brand®

SANITIZING
HAND WIPE

Kills 99.9% of most common germs
that may make you sick
Not for retail sale

ONE WIPE

Distributed by: GOJO Industries, Inc. Akron OH 44309
Purell is a trademark of Warner-Lambert Company LLC